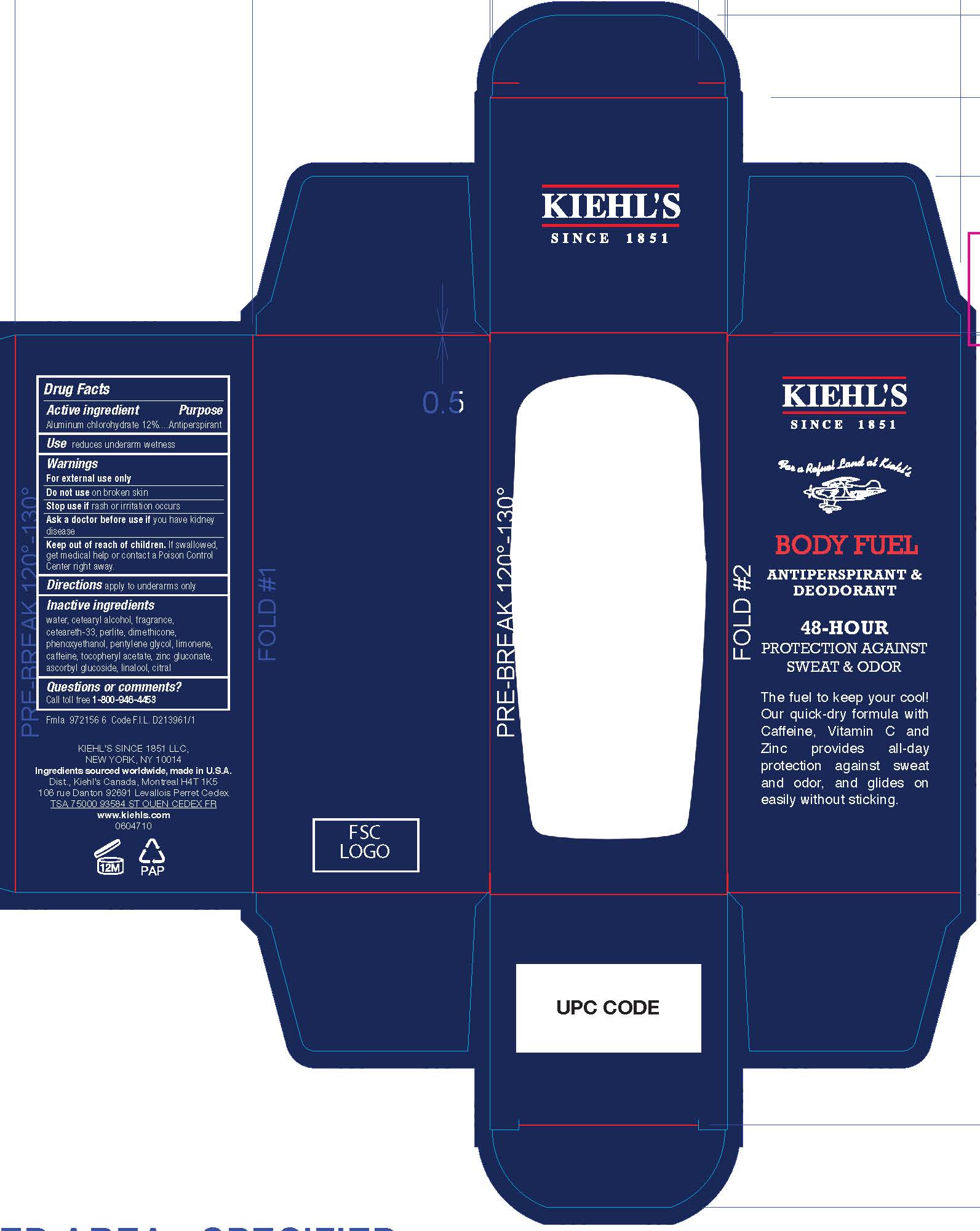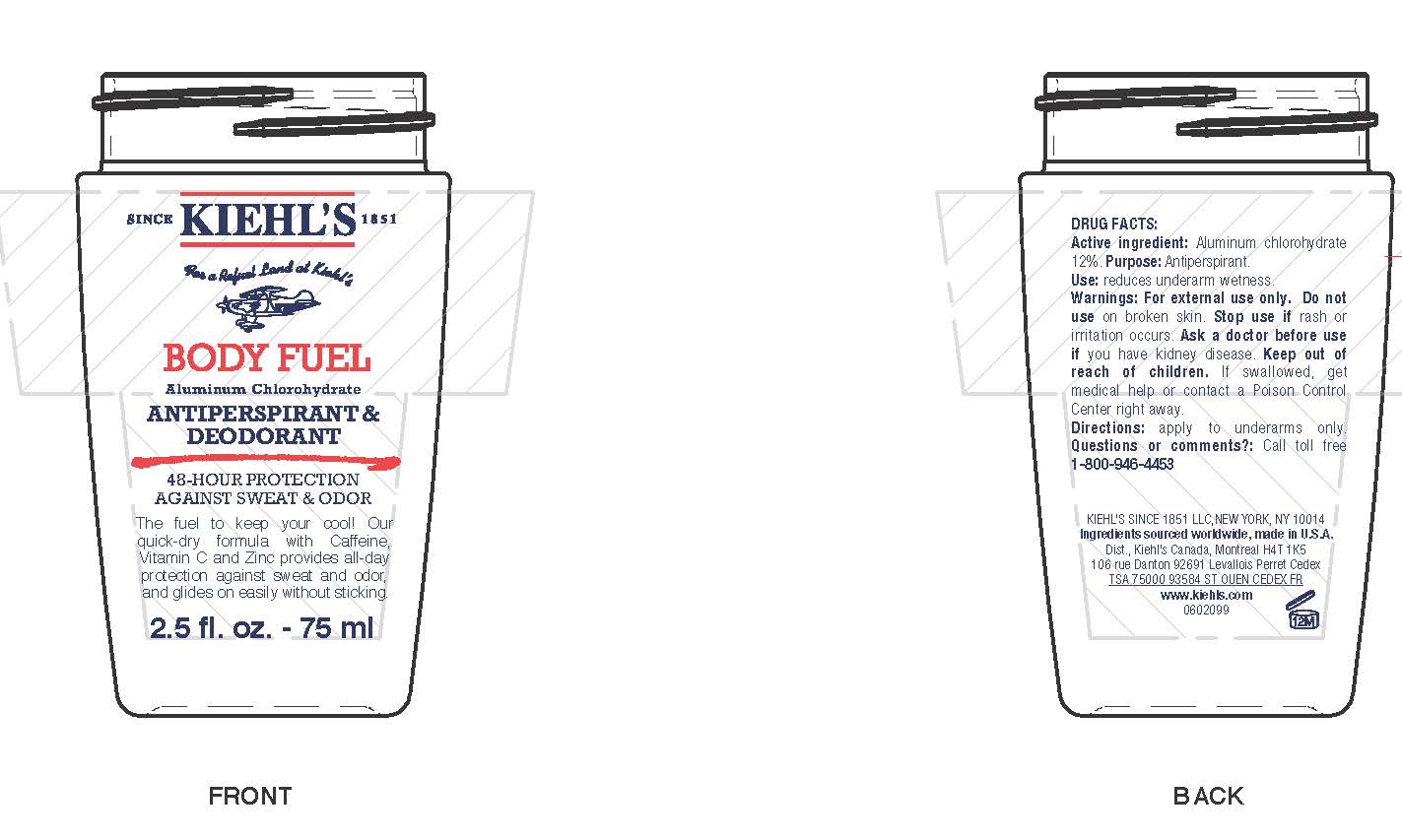 DRUG LABEL: Kiehls Since 1851 Body Fuel Antiperspirant and Deodorant
NDC: 49967-639 | Form: LOTION
Manufacturer: L'Oreal USA Products Inc
Category: otc | Type: HUMAN OTC DRUG LABEL
Date: 20231230

ACTIVE INGREDIENTS: ALUMINUM CHLOROHYDRATE 120 mg/1 mL
INACTIVE INGREDIENTS: WATER; CETOSTEARYL ALCOHOL; CETEARETH-33; PERLITE; DIMETHICONE; PHENOXYETHANOL; PENTYLENE GLYCOL; LIMONENE, (+)-; CAFFEINE; .ALPHA.-TOCOPHEROL ACETATE; ZINC GLUCONATE; ASCORBYL GLUCOSIDE; LINALOOL, (+/-)-; CITRAL

Active ingredient

Aluminum chlorohydrate 12%

Purpose

Antiperspirant

Use

reduces underarm wetness

Warnings

For external use only

Do not use

on broken skin

Stop use if

rash or irritation occurs

Ask a doctor before use if

you have kidney disease

Keep out of reach of children.

If swallowed, get medical help or contact a Poison Control Center right away.

Directions

apply to underarms only

Inactive ingredients

water, cetearyl alcohol, fragrance, ceteareth-33, perlite, dimethicone, phenoxyethanol, pentylene glycol, limonene, caffeine, tocopheryl acetate, zinc gluconate, ascorbyl glucoside, linalool, citral